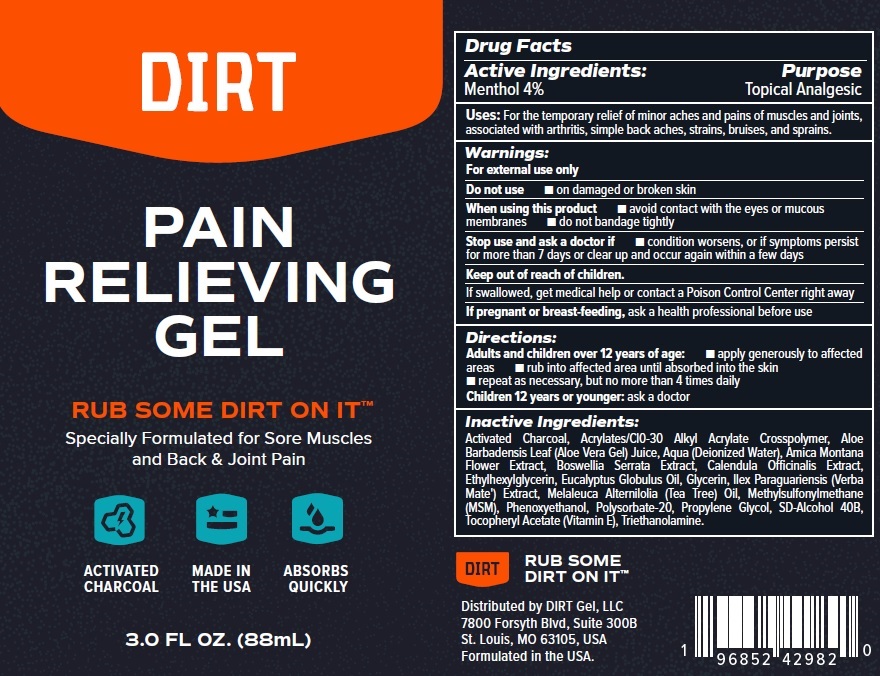 DRUG LABEL: DIRT Pain Relieving Gel
NDC: 83067-463 | Form: GEL
Manufacturer: PURIVITAE, LLC
Category: otc | Type: HUMAN OTC DRUG LABEL
Date: 20231106

ACTIVE INGREDIENTS: MENTHOL 40 mg/1 mL
INACTIVE INGREDIENTS: ACTIVATED CHARCOAL; ALOE VERA LEAF; WATER; ARNICA MONTANA FLOWER; INDIAN FRANKINCENSE; CALENDULA OFFICINALIS FLOWER; ETHYLHEXYLGLYCERIN; EUCALYPTUS OIL; GLYCERIN; ILEX PARAGUARIENSIS LEAF; TEA TREE OIL; DIMETHYL SULFONE; PHENOXYETHANOL; POLYSORBATE 20; PROPYLENE GLYCOL; .ALPHA.-TOCOPHEROL ACETATE; TROLAMINE

DIRT Pain Relieving Gel

Active Ingredients:

Menthol 4%

Purpose

Topical Analgesic

Uses:

For the temporary relief of minor aches and pains of muscles and joints, associated with arthritis, simple back aches, strains, bruises, and sprains.

Warnings:

For external use only

Do not use

- on damaged or broken skin

When using this product

- avoid contact with the eyes or mucous membranes
- do not bandage tightly

Stop use and ask a doctor if

condition worsens, or if symptoms persist for more than 7 days or clear up and occur again within a few days

Keep out of reach of children.

If swallowed, get medical help or contact a Poison Control Center right away

If pregnant or breast-feeding,

ask a health professional before use

Directions:

Adults and children over 12 years of age:

ask a doctor Children 12 years or younger:

- apply generously to affected areas
- rub into affected area until absorbed into the skin
- repeat as necessary, but no more than 4 times daily

Inactive Ingredients:

Activated Charcoal, Acrylates/Cl0-30 Alkyl Acrylate Crosspolymer, Aloe Barbadensis Leaf (Aloe Vera Gel) Juice, Aqua (Deionized Water), Amica Montana Flower Extract, Boswellia Serrata Extract, Calendula Officinalis Extract, Ethylhexylglycerin, Eucalyptus Globulus Oil, Glycerin, llex Paraguariensis (Verba Mate') Extract, Melaleuca Alternilolia (Tea Tree) Oil, Methylsulfonylmethane (MSM), Phenoxyethanol, Polysorbate-20, Propylene Glycol, SD-Alcohol 40B, Tocopheryl Acetate (Vitamin E), Triethanolamine.